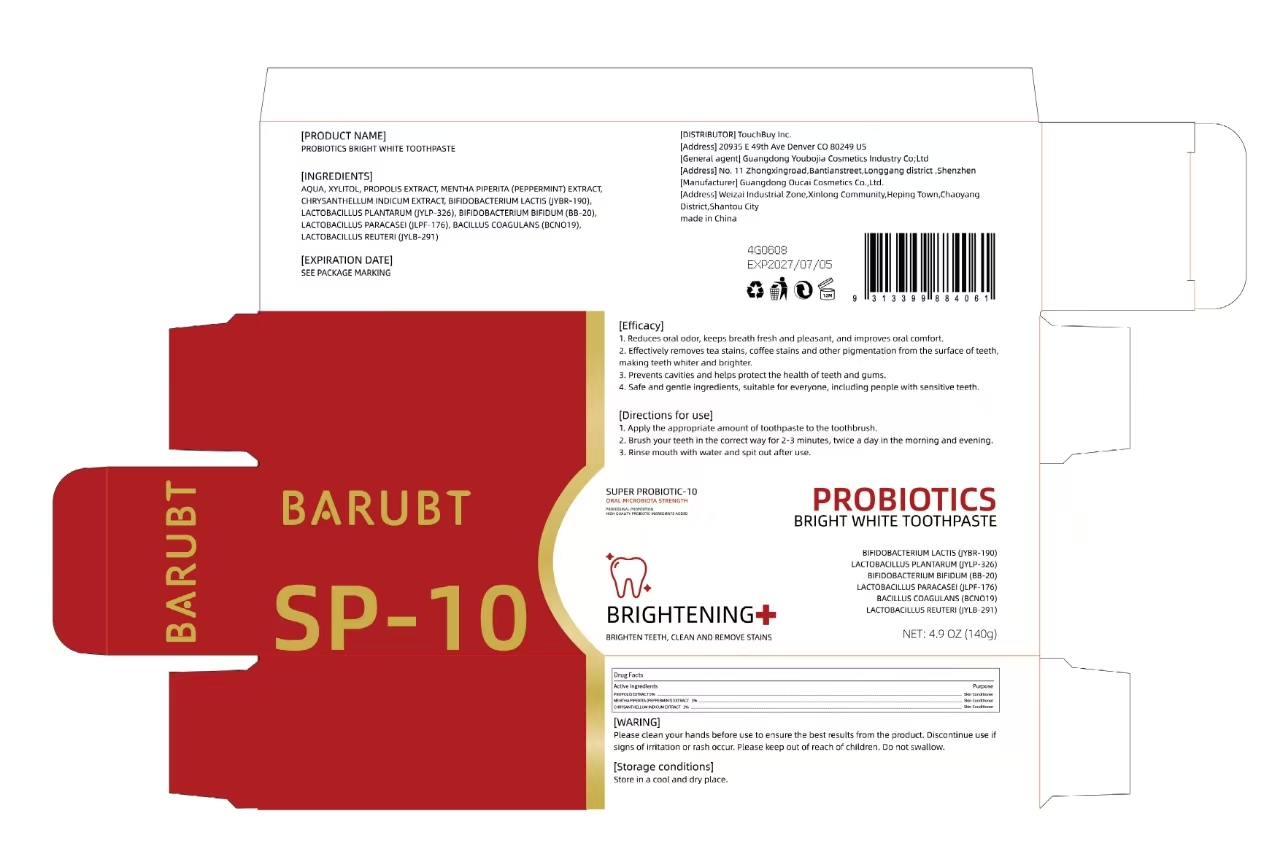 DRUG LABEL: BARUBT Probiotics Bright White Tooth-Paste
NDC: 84712-030 | Form: PASTE
Manufacturer: Guangdong Youbaijia Cosmetic Industry Co., Ltd
Category: otc | Type: HUMAN OTC DRUG LABEL
Date: 20241028

ACTIVE INGREDIENTS: PROPOLIS EXTRACT 7 g/140 g; MENTHA PIPERITA (PEPPERMINT) STEM EXTRACT 1.4 g/140 g; CHRYSANTHELLUM INDICUM FLOWER OIL 1.4 g/140 g
INACTIVE INGREDIENTS: XYLITOL 21 g/140 g

ACTIVE INGREDIENT

PROPOLIS EXTRACT 5%
MENTHA PIPERITA (PEPPERMINT) EXTRACT 1%
CHRYSANTHELLUM INDICUM EXTRACT 1%

INACTIVE INGREDIENT

AQUA
XYLITOL
BIFIDOBACTERIUM LACTIS (JYBR-190)
LACTOBACILLUS PLANTARUM (JYLP-326)
BIFIDOBACTERIUM BIFIDUM (BB-20)
LACTOBACILLUS PARACASEI (JLPF-176)
BACILLUS COAGULANS (BCNO19)
LACTOBACILLUS REUTERI (JYLB-291)

DO NOT USE

Discontinue use if signs of irritation or rash occur

KEEP OUT OF REACH OF CHILDREN

Please keep out of reach of children. Do not swallow.

PURPOSE

Reduces oral odor, keeps breath fresh and pleasant, and improves oral comfort

QUESTIONS

Contact name: Jessie Peng
Company phone number: +1 818 579 7288
Company e-mail: jessie@registeragentllc.com

STOP USE

Discontinue use if signs of irritation or rash occur,

WHEN USING

For external use only. Please clean your hands before use to ensure the best results from the product

WARNINGS

keep out of eyes. Rinse with water to remove.

STORAGE AND HANDLING

Storage conditions:Keep away from light and in a dry place.

INDICATIONS AND USAGE

[Efficacy]
1. Reduces oral odor, keeps breath fresh and pleasant, and improves oral comfort.

2. Effectively removes tea stains, coffee stains and other plgmentation from the surface of teeth
making teeth whiter and brighter.
3. Prevents cavities and helps protect the health of teeth and gums.
4. Safe and gentle ingredients, suitable for everyone, including people with sensitive teeth.

DOSAGE AND ADMINISTRATION

[Directions for use]1. Apply the appropriate amount of loolhpaste to the loothbrush.

2. Brush your teeth in the correct way for 2-3 minutes, twice a day in the morning and evening

3. Rinse mouth with water and spit out after use.